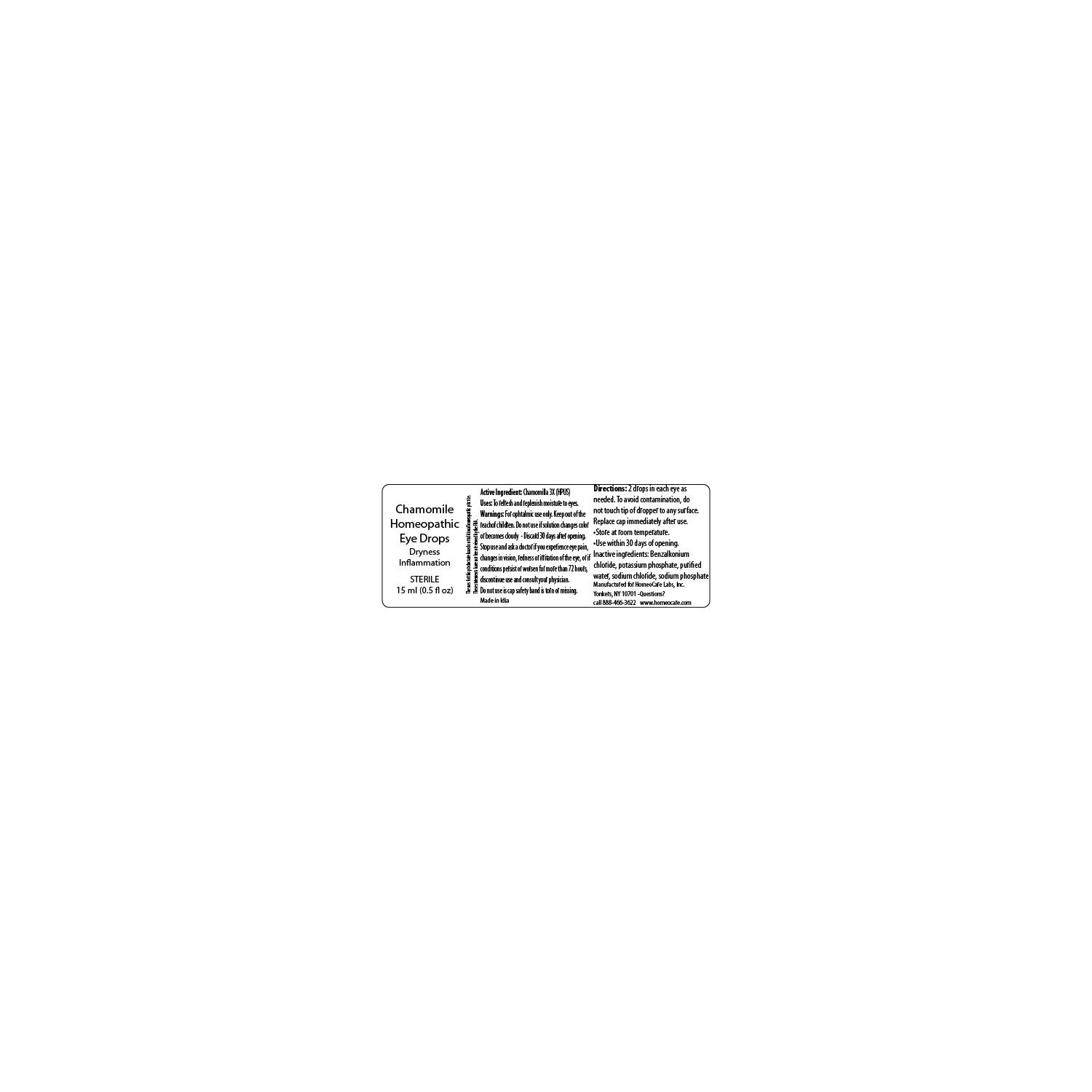 DRUG LABEL: Chamomile Homeopathic Eye Drops
NDC: 61727-346 | Form: SOLUTION/ DROPS
Manufacturer: HomeoCare Laboratories Inc.
Category: homeopathic | Type: HUMAN OTC DRUG LABEL
Date: 20181212

ACTIVE INGREDIENTS: MATRICARIA CHAMOMILLA WHOLE 3 [hp_X]/1 mL
INACTIVE INGREDIENTS: WATER; SODIUM CHLORIDE; SODIUM PHOSPHATE, DIBASIC; BENZALKONIUM CHLORIDE; POTASSIUM PHOSPHATE, UNSPECIFIED FORM

Chamomile Homeopathic Eye Drops

Inactive ingredients

Purified water
Sodium chloride
Sodium phosphate di-basic
Potassium phosphate
Benzalkonium chloride

Purpose

Dryness

Inflammation

DOSAGE AND ADMINISTRATION

Uses To refresh and replenish moisture to eyes.
Directions 2 drops in each eye as needed.
To avoid contamination, do not touch tip of dropper to any surface.
Replace cap immediately after use.
Store at room temperature.
Use within 30 days of opening.

Warnings

For ophtalmic use only. Keep out of the reach of chlidren. Do not use is solution changes color or becomes cloudy. Discard 30 days after opening. Stop use and ask a doctor if you experience eye pain, changes in vision, redness or irritation of the eye. If conditions persist or worsen for more than 72 hours, discontinue use and consult your physician.

Do not use is cap safety band is torn or missing.

Active Ingredients

Chamomilla 3X HPUS

INDICATIONS AND USAGE

Uses To refresh and replenish moisture to eyes.
Directions 2 drops in each eye as needed.
To avoid contamination, do not touch tip of dropper to any surface.
Replace cap immediately after use.
Store at room temperature.
Use within 30 days of opening.

Keep out of the reach of children.

Label

SterileEyeDropsSri.jpg

Chamomile Homeopathic Eye Drops